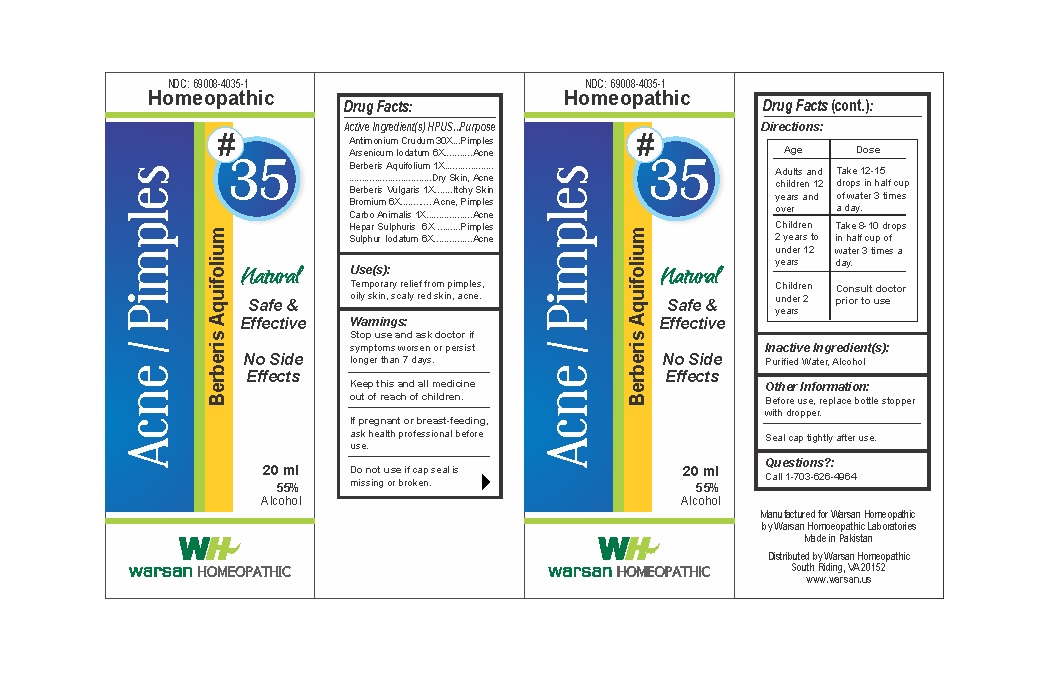 DRUG LABEL: Combination Remedy 35 - Acne Pimples
NDC: 69008-4035 | Form: SOLUTION/ DROPS
Manufacturer: Warsan Homoeopathic Laboratories
Category: homeopathic | Type: HUMAN OTC DRUG LABEL
Date: 20171225

ACTIVE INGREDIENTS: SULFUR IODIDE 6 [hp_X]/1 mL; MAHONIA AQUIFOLIUM ROOT BARK 1 [hp_X]/1 mL; BERBERIS VULGARIS ROOT BARK 1 [hp_X]/1 mL; ANTIMONY TRISULFIDE 30 [hp_X]/1 mL; CARBO ANIMALIS 1 [hp_X]/1 mL; CALCIUM SULFIDE 6 [hp_X]/1 mL; ARSENIC TRIIODIDE 6 [hp_X]/1 mL; BROMINE 6 [hp_X]/1 mL
INACTIVE INGREDIENTS: ALCOHOL; WATER

Stop use and ask doctor if symptoms worsen or persist longer than 7 days.

If pregnant or breast-feeding, ask health professional before use.

Do not use if tamper evident seal is missing or broken.

Keep out of reach of children.

ACTIVE INGREDIENT

Antimonium Crudum 30X

Arsenicum Iodatum 6X

Berberis Aquifolium 1X

Berberis Vulgaris 1X

Bromium 6X

Carbo Animalis 1X

Hepar Sulphuris 6X

Sulphur Iodatum 6X

PURPOSE

Temporary relief from pimples, oily skin, scaly red skin, acne

INACTIVE INGREDIENT

Purified Water

Alcohol

DOSAGE AND ADMINISTRATION

Adults and children 12 years and older: Take 10-15 drops in half cup of water 3 times a day.

Children 2 years to under 12 years: Take 8-10 drops in half cup of water of 3 times a day.

Children under 2 years: Consult doctor prior to use.

INDICATIONS AND USAGE

Temporary relief from pimples, oily skin, scaly red skin, acne